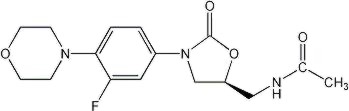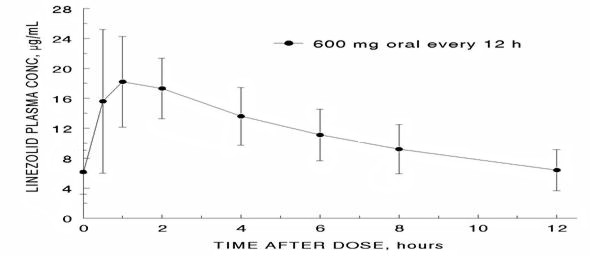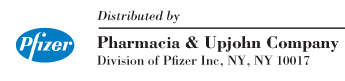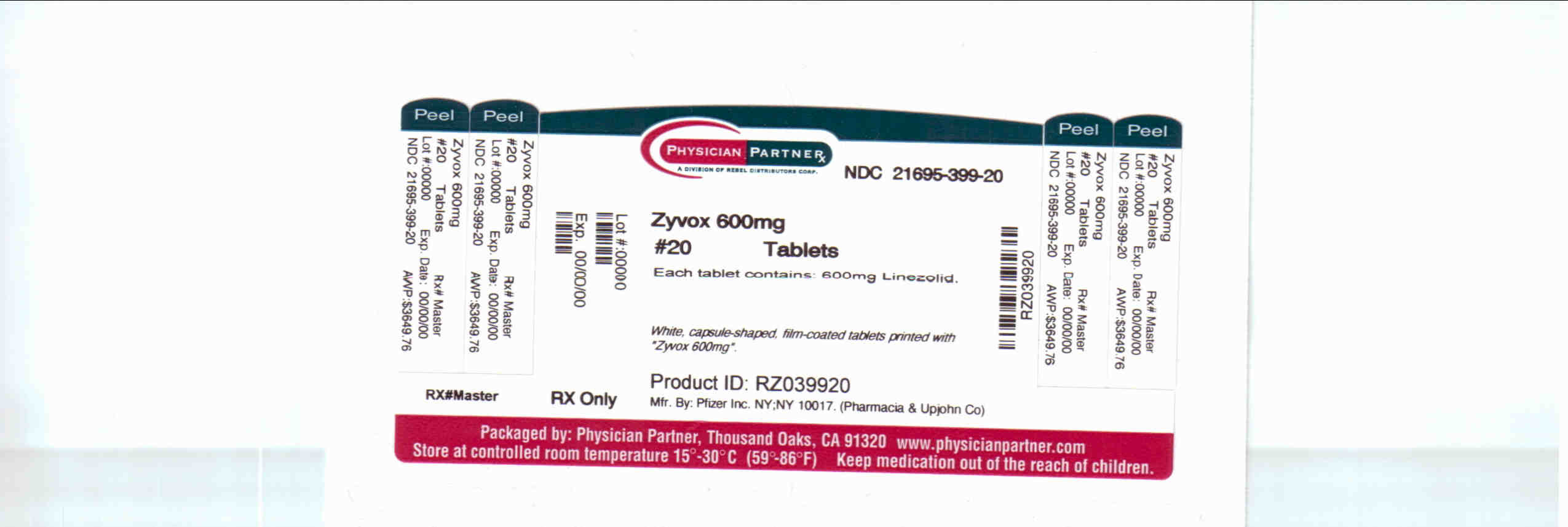 DRUG LABEL: Zyvox
NDC: 21695-399 | Form: TABLET, FILM COATED
Manufacturer: Rebel Distributors Corp
Category: prescription | Type: HUMAN PRESCRIPTION DRUG LABEL
Date: 20101222

ACTIVE INGREDIENTS: linezolid 600 mg/1 1
INACTIVE INGREDIENTS: starch, corn; cellulose, microcrystalline; hydroxypropyl cellulose; magnesium stearate; HYPROMELLOSES; polyethylene glycol; titanium dioxide; carnauba wax

ZYVOX®
(linezolid) injection
(linezolid) tablets
(linezolid) for oral suspension

To reduce the development of drug-resistant bacteria and maintain the effectiveness of ZYVOX formulations and other antibacterial drugs, ZYVOX should be used only to treat or prevent infections that are proven or strongly suspected to be caused by bacteria.

DESCRIPTION

ZYVOX I.V. Injection, ZYVOX Tablets, and ZYVOX for Oral Suspension contain linezolid, which is a synthetic antibacterial agent of the oxazolidinone class. The chemical name for linezolid is (S)-N-[[3-[3-Fluoro-4-(4-morpholinyl)phenyl]-2-oxo-5-oxazolidinyl]methyl]-acetamide.

The empirical formula is C16H20FN3O4. Its molecular weight is 337.35, and its chemical structure is represented below:

ZYVOX I.V. Injection is supplied as a ready-to-use sterile isotonic solution for intravenous infusion. Each mL contains 2 mg of linezolid. Inactive ingredients are sodium citrate, citric acid, and dextrose in an aqueous vehicle for intravenous administration. The sodium (Na^+) content is 0.38 mg/mL (5 mEq per 300-mL bag; 3.3 mEq per 200-mL bag; and 1.7 mEq per 100-mL bag).

ZYVOX Tablets for oral administration contain 400 mg or 600 mg linezolid as film-coated compressed tablets. Inactive ingredients are corn starch, microcrystalline cellulose, hydroxypropylcellulose, sodium starch glycolate, magnesium stearate, hypromellose, polyethylene glycol, titanium dioxide, and carnauba wax. The sodium (Na^+) content is 1.95 mg per 400-mg tablet and 2.92 mg per 600-mg tablet (0.1 mEq per tablet, regardless of strength).

ZYVOX for Oral Suspension is supplied as an orange-flavored granule/powder for constitution into a suspension for oral administration. Following constitution, each 5 mL contains 100 mg of linezolid. Inactive ingredients are sucrose, citric acid, sodium citrate, microcrystalline cellulose and carboxymethylcellulose sodium, aspartame, xanthan gum, mannitol, sodium benzoate, colloidal silicon dioxide, sodium chloride, and flavors (see PRECAUTIONS, Information for Patients). The sodium (Na^+) content is 8.52 mg per 5 mL (0.4 mEq per 5 mL).

CLINICAL PHARMACOLOGY

Pharmacokinetics

The mean pharmacokinetic parameters of linezolid in adults after single and multiple oral and intravenous (IV) doses are summarized in Table 1. Plasma concentrations of linezolid at steady-state after oral doses of 600 mg given every 12 hours (q12h) are shown in Figure 1.

Table 1. Mean (Standard Deviation) Pharmacokinetic Parameters of Linezolid in Adults
Dose of Linezolid | Cmax µg/mL | Cmin µg/mL | Tmax hrs | AUC [AUC for single dose = AUC0–∞; for multiple-dose = AUC0–τ] µg ∙ h/mL | t1/2 hrs | CL mL/min
400 mg tablet single dose [Data dose-normalized from 375 mg] every 12 hours | 8.10 (1.83) 11.00 (4.37) | --- 3.08 (2.25) | 1.52 (1.01) 1.12 (0.47) | 55.10 (25.00) 73.40 (33.50) | 5.20 (1.50) 4.69 (1.70) | 146 (67) 110 (49)
600 mg tablet single dose every 12 hours | 12.70 (3.96) 21.20 (5.78) | --- 6.15 (2.94) | 1.28 (0.66) 1.03 (0.62) | 91.40 (39.30) 138.00 (42.10) | 4.26 (1.65) 5.40 (2.06) | 127 (48) 80 (29)
600 mg IV injection [Data dose-normalized from 625 mg, IV dose was given as 0.5-hour infusion.] single dose every 12 hours | 12.90 (1.60) 15.10 (2.52) | --- 3.68 (2.36) | 0.50 (0.10) 0.51 (0.03) | 80.20 (33.30) 89.70 (31.00) | 4.40 (2.40) 4.80 (1.70) | 138 (39) 123 (40)
600 mg oral suspension single dose | 11.00 (2.76) | --- | 0.97 (0.88) | 80.80 (35.10) | 4.60 (1.71) | 141 (45)
Cmax = Maximum plasma concentration; Cmin = Minimum plasma concentration; Tmax = Time to Cmax; AUC = Area under concentration-time curve; t1/2 = Elimination half-life; CL = Systemic clearance

Figure 1. Plasma Concentrations of Linezolid in Adults at Steady-State Following Oral Dosing Every 12 Hours (Mean ± Standard Deviation, n=16)

Absorption

Linezolid is rapidly and extensively absorbed after oral dosing. Maximum plasma concentrations are reached approximately 1 to 2 hours after dosing, and the absolute bioavailability is approximately 100%. Therefore, linezolid may be given orally or intravenously without dose adjustment.

Linezolid may be administered without regard to the timing of meals. The time to reach the maximum concentration is delayed from 1.5 hours to 2.2 hours and Cmax is decreased by about 17% when high fat food is given with linezolid. However, the total exposure measured as AUC0-∞ values is similar under both conditions.

Distribution

Animal and human pharmacokinetic studies have demonstrated that linezolid readily distributes to well-perfused tissues. The plasma protein binding of linezolid is approximately 31% and is concentration-independent. The volume of distribution of linezolid at steady-state averaged 40 to 50 liters in healthy adult volunteers.

Linezolid concentrations have been determined in various fluids from a limited number of subjects in Phase 1 volunteer studies following multiple dosing of linezolid. The ratio of linezolid in saliva relative to plasma was 1.2 to 1 and for sweat relative to plasma was 0.55 to 1.

Metabolism

Linezolid is primarily metabolized by oxidation of the morpholine ring, which results in two inactive ring-opened carboxylic acid metabolites: the aminoethoxyacetic acid metabolite (A), and the hydroxyethyl glycine metabolite (B). Formation of metabolite A is presumed to be formed via an enzymatic pathway whereas metabolite B is mediated by a non-enzymatic chemical oxidation mechanism in vitro. In vitro studies have demonstrated that linezolid is minimally metabolized and may be mediated by human cytochrome P450. However, the metabolic pathway of linezolid is not fully understood.

Excretion

Nonrenal clearance accounts for approximately 65% of the total clearance of linezolid. Under steady-state conditions, approximately 30% of the dose appears in the urine as linezolid, 40% as metabolite B, and 10% as metabolite A. The renal clearance of linezolid is low (average 40 mL/min) and suggests net tubular reabsorption. Virtually no linezolid appears in the feces, while approximately 6% of the dose appears in the feces as metabolite B, and 3% as metabolite A.

A small degree of nonlinearity in clearance was observed with increasing doses of linezolid, which appears to be due to lower renal and nonrenal clearance of linezolid at higher concentrations. However, the difference in clearance was small and was not reflected in the apparent elimination half-life.

Special Populations

Geriatric

The pharmacokinetics of linezolid are not significantly altered in elderly patients (65 years or older). Therefore, dose adjustment for geriatric patients is not necessary.

Pediatric

The pharmacokinetics of linezolid following a single IV dose were investigated in pediatric patients ranging in age from birth through 17 years (including premature and full-term neonates), in healthy adolescent subjects ranging in age from 12 through 17 years, and in pediatric patients ranging in age from 1 week through 12 years. The pharmacokinetic parameters of linezolid are summarized in Table 2 for the pediatric populations studied and healthy adult subjects after administration of single IV doses.

The Cmax and the volume of distribution (Vss) of linezolid are similar regardless of age in pediatric patients. However, clearance of linezolid varies as a function of age. With the exclusion of pre-term neonates less than one week of age, clearance is most rapid in the youngest age groups ranging from >1 week old to 11 years, resulting in lower single-dose systemic exposure (AUC) and shorter half-life as compared with adults. As age of pediatric patients increases, the clearance of linezolid gradually decreases, and by adolescence mean clearance values approach those observed for the adult population. There is wider inter-subject variability in linezolid clearance and systemic drug exposure (AUC) across all pediatric age groups as compared with adults.

Similar mean daily AUC values were observed in pediatric patients from birth to 11 years of age dosed every 8 hours (q8h) relative to adolescents or adults dosed every 12 hours (q12h). Therefore, the dosage for pediatric patients up to 11 years of age should be 10 mg/kg q8h. Pediatric patients 12 years and older should receive 600 mg q12h (see DOSAGE AND ADMINISTRATION).

Table 2. Pharmacokinetic Parameters of Linezolid in Pediatrics and Adults Following a Single Intravenous Infusion of 10 mg/kg or 600 mg Linezolid (Mean: (%CV); [Min, Max Values])
Age Group | Cmax µg/mL | Vss L/kg | AUC [AUC = Single dose AUC0–∞] µg • h/mL | t 1/2 hrs | CL mL/min/kg
Neonatal Patients Pre-term [In this data set, "pre-term" is defined as <34 weeks gestational age (Note: Only 1 patient enrolled was pre-term with a postnatal age between 1 week and 28 days)] < 1 week (N=9) [Dose of 10 mg/kg] | 12.7 (30%) [9.6, 22.2] | 0.81 (24%) [0.43, 1.05] | 108 (47%) [41, 191] | 5.6 (46%) [2.4, 9.8] | 2.0 (52%) [0.9, 4.0]
Full-term [In this data set, "full-term" is defined as ≥34 weeks gestational age] < 1 week (N=10) | 11.5 (24%) [8.0, 18.3] | 0.78 (20%) [0.45, 0.96] | 55 (47%) [19, 103] | 3.0 (55%) [1.3, 6.1] | 3.8 (55%) [1.5, 8.8]
Full-term ≥ 1 week to ≤ 28 days (N=10) | 12.9 (28%) [7.7, 21.6] | 0.66 (29%) [0.35, 1.06] | 34 (21%) [23, 50] | 1.5 (17%) [1.2, 1.9] | 5.1 (22%) [3.3, 7.2]
Infant Patients > 28 days to < 3 Months (N=12) | 11.0 (27%) [7.2, 18.0] | 0.79 (26%) [0.42, 1.08] | 33 (26%) [17, 48] | 1.8 (28%) [1.2, 2.8] | 5.4 (32%) [3.5, 9.9]
Pediatric Patients 3 months through 11 years (N=59) | 15.1 (30%) [6.8, 36.7] | 0.69 (28%) [0.31, 1.50] | 58 (54%) [19, 153] | 2.9 (53%) [0.9, 8.0] | 3.8 (53%) [1.0, 8.5]
Adolescent Subjects and Patients 12 through 17 years [Dose of 600 mg or 10 mg/kg up to a maximum of 600 mg] (N=36) | 16.7 (24%) [9.9, 28.9] | 0.61 (15%) [0.44, 0.79] | 95 (44%) [32, 178] | 4.1 (46%) [1.3, 8.1] | 2.1 (53%) [0.9, 5.2]
Adult Subjects [Dose normalized to 600 mg] (N= 29) | 12.5 (21%) [8.2, 19.3] | 0.65 (16%) [0.45, 0.84] | 91 (33%) [53, 155] | 4.9 (35%) [1.8, 8.3] | 1.7 (34%) [0.9, 3.3]
Cmax = Maximum plasma concentration; Vss= Volume of distribution; AUC = Area under concentration-time curve; t1/2 = Apparent elimination half-life; CL = Systemic clearance normalized for body weight

Gender

Females have a slightly lower volume of distribution of linezolid than males. Plasma concentrations are higher in females than in males, which is partly due to body weight differences. After a 600-mg dose, mean oral clearance is approximately 38% lower in females than in males. However, there are no significant gender differences in mean apparent elimination-rate constant or half-life. Thus, drug exposure in females is not expected to substantially increase beyond levels known to be well tolerated. Therefore, dose adjustment by gender does not appear to be necessary.

Renal Insufficiency

The pharmacokinetics of the parent drug, linezolid, are not altered in patients with any degree of renal insufficiency; however, the two primary metabolites of linezolid may accumulate in patients with renal insufficiency, with the amount of accumulation increasing with the severity of renal dysfunction (see Table 3). The clinical significance of accumulation of these two metabolites has not been determined in patients with severe renal insufficiency. Because similar plasma concentrations of linezolid are achieved regardless of renal function, no dose adjustment is recommended for patients with renal insufficiency. However, given the absence of information on the clinical significance of accumulation of the primary metabolites, use of linezolid in patients with renal insufficiency should be weighed against the potential risks of accumulation of these metabolites. Both linezolid and the two metabolites are eliminated by dialysis. No information is available on the effect of peritoneal dialysis on the pharmacokinetics of linezolid. Approximately 30% of a dose was eliminated in a 3-hour dialysis session beginning 3 hours after the dose of linezolid was administered; therefore, linezolid should be given after hemodialysis.

Table 3. Mean (Standard Deviation) AUCs and Elimination Half-lives of Linezolid and Metabolites A and B in Patients with Varying Degrees of Renal Insufficiency After a Single 600-mg Oral Dose of Linezolid
Parameter | Healthy Subjects CLCR > 80 mL/min | Moderate Renal Impairment 30 < CLCR < 80 mL/min | Severe Renal Impairment 10 < CLCR < 30 mL/min | Hemodialysis-Dependent
Parameter | Healthy Subjects CLCR > 80 mL/min | Moderate Renal Impairment 30 < CLCR < 80 mL/min | Severe Renal Impairment 10 < CLCR < 30 mL/min | Off Dialysis [between hemodialysis sessions] | On Dialysis
Linezolid
AUC0–∞, µg h/mL | 110 (22) | 128 (53) | 127 (66) | 141 (45) | 83 (23)
t1/2, hours | 6.4 (2.2) | 6.1 (1.7) | 7.1 (3.7) | 8.4 (2.7) | 7.0 (1.8)
Metabolite A
AUC0–48, µg h/mL | 7.6 (1.9) | 11.7 (4.3) | 56.5 (30.6) | 185 (124) | 68.8 (23.9)
t1/2, hours | 6.3 (2.1) | 6.6 (2.3) | 9.0 (4.6) | NA | NA
Metabolite B
AUC0–48, µg h/mL | 30.5 (6.2) | 51.1 (38.5) | 203 (92) | 467 (102) | 239 (44)
t1/2, hours | 6.6 (2.7) | 9.9 (7.4) | 11.0 (3.9) | NA | NA
NA = Not applicable

Hepatic Insufficiency

The pharmacokinetics of linezolid are not altered in patients (n=7) with mild-to-moderate hepatic insufficiency (Child-Pugh class A or B). On the basis of the available information, no dose adjustment is recommended for patients with mild-to-moderate hepatic insufficiency. The pharmacokinetics of linezolid in patients with severe hepatic insufficiency have not been evaluated.

Drug-Drug Interactions

Drugs Metabolized by Cytochrome P450

Linezolid is not an inducer of cytochrome P450 (CYP450) in rats. In addition, linezolid does not inhibit the activities of clinically significant human CYP isoforms (e.g., 1A2, 2C9, 2C19, 2D6, 2E1, 3A4). Therefore, linezolid is not expected to affect the pharmacokinetics of other drugs metabolized by these major enzymes. Concurrent administration of linezolid does not substantially alter the pharmacokinetic characteristics of (S)-warfarin, which is extensively metabolized by CYP2C9. Drugs such as warfarin and phenytoin, which are CYP2C9 substrates, may be given with linezolid without changes in dosage regimen.

Antibiotics

Aztreonam: The pharmacokinetics of linezolid or aztreonam are not altered when administered together.

Gentamicin: The pharmacokinetics of linezolid or gentamicin are not altered when administered together.

Rifampin: The effect of rifampin on the pharmacokinetics of linezolid was evaluated in a study of 16 healthy adult males. Volunteers were administered oral linezolid 600 mg twice daily for 5 doses with and without rifampin 600 mg once daily for 8 days. Co-administration of rifampin with linezolid resulted in a 21% decrease in linezolid Cmax [90% CI, 15% – 27%] and a 32% decrease in linezolid AUC0–12 [90% CI, 27% – 37%]. The mechanism of this interaction is not fully understood and may be related to the induction of hepatic enzymes (see PRECAUTIONS, Drug Interactions).

Monoamine Oxidase Inhibition

Linezolid is a reversible, nonselective inhibitor of monoamine oxidase. Therefore, linezolid has the potential for interaction with adrenergic and serotonergic agents.

Adrenergic Agents: A significant pressor response has been observed in normal adult subjects receiving linezolid and tyramine doses of more than 100 mg. Therefore, patients receiving linezolid need to avoid consuming large amounts of foods or beverages with high tyramine content (see PRECAUTIONS, Information for Patients).

A reversible enhancement of the pressor response of either pseudoephedrine HCl (PSE) or phenylpropanolamine HCl (PPA) is observed when linezolid is administered to healthy normotensive subjects (see PRECAUTIONS, Drug Interactions). A similar study has not been conducted in hypertensive patients. The interaction studies conducted in normotensive subjects evaluated the blood pressure and heart rate effects of placebo, PPA or PSE alone, linezolid alone, and the combination of steady-state linezolid (600 mg q12h for 3 days) with two doses of PPA (25 mg) or PSE (60 mg) given 4 hours apart. Heart rate was not affected by any of the treatments. Blood pressure was increased with both combination treatments. Maximum blood pressure levels were seen 2 to 3 hours after the second dose of PPA or PSE, and returned to baseline 2 to 3 hours after peak. The results of the PPA study follow, showing the mean (and range) maximum systolic blood pressure in mm Hg: placebo = 121 (103 to 158); linezolid alone = 120 (107 to 135); PPA alone = 125 (106 to 139); PPA with linezolid = 147 (129 to 176). The results from the PSE study were similar to those in the PPA study. The mean maximum increase in systolic blood pressure over baseline was 32 mm Hg (range: 20–52 mm Hg) and 38 mm Hg (range: 18–79 mm Hg) during co-administration of linezolid with pseudoephedrine or phenylpropanolamine, respectively.

Serotonergic Agents: The potential drug-drug interaction with dextromethorphan was studied in healthy volunteers. Subjects were administered dextromethorphan (two 20-mg doses given 4 hours apart) with or without linezolid. No serotonin syndrome effects (confusion, delirium, restlessness, tremors, blushing, diaphoresis, hyperpyrexia) have been observed in normal subjects receiving linezolid and dextromethorphan.

MICROBIOLOGY

Linezolid is a synthetic antibacterial agent of a new class of antibiotics, the oxazolidinones, which has clinical utility in the treatment of infections caused by aerobic Gram-positive bacteria. The in vitro spectrum of activity of linezolid also includes certain Gram-negative bacteria and anaerobic bacteria. Linezolid inhibits bacterial protein synthesis through a mechanism of action different from that of other antibacterial agents; therefore, cross-resistance between linezolid and other classes of antibiotics is unlikely. Linezolid binds to a site on the bacterial 23S ribosomal RNA of the 50S subunit and prevents the formation of a functional 70S initiation complex, which is an essential component of the bacterial translation process. The results of time-kill studies have shown linezolid to be bacteriostatic against enterococci and staphylococci. For streptococci, linezolid was found to be bactericidal for the majority of strains.

In clinical trials, resistance to linezolid developed in 6 patients infected with Enterococcus faecium (4 patients received 200 mg q12h, lower than the recommended dose, and 2 patients received 600 mg q12h). In a compassionate use program, resistance to linezolid developed in 8 patients with E. faecium and in 1 patient with Enterococcus faecalis. All patients had either unremoved prosthetic devices or undrained abscesses. Resistance to linezolid occurs in vitro at a frequency of 1 x 10 ^-9 to 1 x 10 ^-11. In vitro studies have shown that point mutations in the 23S rRNA are associated with linezolid resistance. Reports of vancomycin-resistant E. faecium becoming resistant to linezolid during its clinical use have been published.^1 In one report nosocomial spread of vancomycin- and linezolid-resistant E. faecium occurred ^2. There has been a report of Staphylococcus aureus (methicillin-resistant) developing resistance to linezolid during its clinical use.^3 The linezolid resistance in these organisms was associated with a point mutation in the 23S rRNA (substitution of thymine for guanine at position 2576) of the organism. When antibiotic-resistant organisms are encountered in the hospital, it is important to emphasize infection control policies.^(4, 5) Resistance to linezolid has not been reported in Streptococcus spp., including Streptococcus pneumoniae.

In vitro studies have demonstrated additivity or indifference between linezolid and vancomycin, gentamicin, rifampin, imipenem-cilastatin, aztreonam, ampicillin, or streptomycin.

Linezolid has been shown to be active against most isolates of the following microorganisms, both in vitro and in clinical infections, as described in the INDICATIONS AND USAGE section.

Aerobic and facultative Gram-positive microorganisms

Enterococcus faecium (vancomycin-resistant strains only)
Staphylococcus aureus (including methicillin-resistant strains)
Streptococcus agalactiae
Streptococcus pneumoniae (including multi-drug resistant isolates [MDRSP] [MDRSP refers to isolates resistant to two or more of the following antibiotics: penicillin, second-generation cephalosporins, macrolides, tetracycline, and trimethoprim/sulfamethoxazole.])
Streptococcus pyogenes

The following in vitro data are available, but their clinical significance is unknown. At least 90% of the following microorganisms exhibit an in vitro minimum inhibitory concentration (MIC) less than or equal to the susceptible breakpoint for linezolid. However, the safety and effectiveness of linezolid in treating clinical infections due to these microorganisms have not been established in adequate and well-controlled clinical trials.

Aerobic and facultative Gram-positive microorganisms

Enterococcus faecalis (including vancomycin-resistant strains)
Enterococcus faecium (vancomycin-susceptible strains)
Staphylococcus epidermidis (including methicillin-resistant strains)
Staphylococcus haemolyticus
Viridans group streptococci

Aerobic and facultative Gram-negative microorganisms

Pasteurella multocida

Susceptibility Testing Methods

NOTE: Susceptibility testing by dilution methods requires the use of linezolid susceptibility powder.

When available, the results of in vitro susceptibility tests should be provided to the physician as periodic reports which describe the susceptibility profile of nosocomial and community-acquired pathogens. These reports should aid the physician in selecting the most effective antimicrobial.

Dilution Techniques

Quantitative methods are used to determine antimicrobial minimum inhibitory concentrations (MICs). These MICs provide estimates of the susceptibility of bacteria to antimicrobial compounds. The MICs should be determined using a standardized procedure. Standardized procedures are based on a dilution method ^6,7 (broth or agar) or equivalent with standardized inoculum concentrations and standardized concentrations of linezolid powder. The MIC values should be interpreted according to criteria provided in Table 4.

Diffusion Techniques

Quantitative methods that require measurement of zone diameters also provide reproducible estimates of the susceptibility of bacteria to antimicrobial compounds. One such standardized procedure ^7,^8 requires the use of standardized inoculum concentrations. This procedure uses paper disks impregnated with 30 µg of linezolid to test the susceptibility of microorganisms to linezolid. The disk diffusion interpretive criteria are provided in Table 4.

Table 4. Susceptibility Interpretive Criteria for Linezolid
Pathogen | Susceptibility Interpretive Criteria
Pathogen | Minimal Inhibitory Concentrations (MIC in µg/mL) |  |  | Disk Diffusion (Zone Diameters in mm)
Pathogen | S | I | R | S | I | R
Enterococcus spp | ≤ 2 | 4 | ≥8 | ≥ 23 | 21–22 | ≤20
Staphylococcus spp [The current absence of data on resistant strains precludes defining any categories other than "Susceptible." Strains yielding test results suggestive of a "nonsusceptible" category should be retested, and if the result is confirmed, the isolate should be submitted to a reference laboratory for further testing.] | ≤4 | --- | --- | ≥ 21 | --- | ---
Streptococcus pneumoniae | ≤2 [These interpretive standards for S. pneumoniae and Streptococcus spp. other than S. pneumoniae are applicable only to tests performed by broth microdilution using cation-adjusted Mueller-Hinton broth with 2 to 5% lysed horse blood inoculated with a direct colony suspension and incubated in ambient air at 35°C for 20 to 24 hours.] | --- | --- | ≥ 21 [These zone diameter interpretive standards are applicable only to tests performed using Mueller-Hinton agar supplemented with 5% defibrinated sheep blood inoculated with a direct colony suspension and incubated in 5% CO2 at 35°C for 20 to 24 hours.] | --- | ---
Streptococcus spp other than S pneumoniae | ≤2 | --- | --- | ≥ 21 | --- | ---

A report of "Susceptible" indicates that the pathogen is likely to be inhibited if the antimicrobial compound in the blood reaches the concentrations usually achievable. A report of "Intermediate" indicates that the result should be considered equivocal, and, if the microorganism is not fully susceptible to alternative, clinically feasible drugs, the test should be repeated. This category implies possible clinical applicability in body sites where the drug is physiologically concentrated or in situations where high dosage of drug can be used. This category also provides a buffer zone which prevents small uncontrolled technical factors from causing major discrepancies in interpretation. A report of "Resistant" indicates that the pathogen is not likely to be inhibited if the antimicrobial compound in the blood reaches the concentrations usually achievable; other therapy should be selected.

Quality Control

Standardized susceptibility test procedures require the use of quality control microorganisms to control the technical aspects of the test procedures. Standard linezolid powder should provide the following range of values noted in Table 5. NOTE: Quality control microorganisms are specific strains of organisms with intrinsic biological properties relating to resistance mechanisms and their genetic expression within bacteria; the specific strains used for microbiological quality control are not clinically significant.

Table 5. Acceptable Quality Control Ranges for Linezolid to be Used in Validation of Susceptibility Test Results
QC Strain | Acceptable Quality Control Ranges
QC Strain | Minimum Inhibitory Concentration (MIC in µg/mL) | Disk Diffusion (Zone Diameters in mm)
Enterococcus faecalis ATCC 29212 | 1 – 4 | Not applicable
Staphylococcus aureus ATCC 29213 | 1 – 4 | Not applicable
Staphylococcus aureus ATCC 25923 | Not applicable | 25 – 32
Streptococcus pneumoniae ATCC 49619 [This organism may be used for validation of susceptibility test results when testing Streptococcus spp. other than S. pneumoniae.] | 0.50 – 2 [This quality control range for S. pneumoniae is applicable only to tests performed by broth microdilution using cation-adjusted Mueller-Hinton broth with 2 to 5% lysed horse blood inoculated with a direct colony suspension and incubated in ambient air at 35°C for 20 to 24 hours.] | 25 – 34 [This quality control zone diameter range is applicable only to tests performed using Mueller-Hinton agar supplemented with 5% defibrinated sheep blood inoculated with a direct colony suspension and incubated in 5% CO2 at 35°C for 20 to 24 hours.]

INDICATIONS AND USAGE

ZYVOX formulations are indicated in the treatment of the following infections caused by susceptible strains of the designated microorganisms (see PRECAUTIONS, Pediatric Use and DOSAGE AND ADMINISTRATION and CLINICAL STUDIES). Linezolid is not indicated for the treatment of Gram-negative infections. It is critical that specific Gram-negative therapy be initiated immediately if a concomitant Gram-negative pathogen is documented or suspected (see WARNINGS).

Vancomycin-Resistant Enterococcus faecium infections, including cases with concurrent bacteremia. (see CLINICAL STUDIES)

Nosocomial pneumonia caused by Staphylococcus aureus (methicillin-susceptible and -resistant strains), or Streptococcus pneumoniae (including multi-drug resistant strains [MDRSP]).

Complicated skin and skin structure infections, including diabetic foot infections, without concomitant osteomyelitis, caused by Staphylococcus aureus (methicillin-susceptible and -resistant strains), Streptococcus pyogenes, or Streptococcus agalactiae. ZYVOX has not been studied in the treatment of decubitus ulcers.

Uncomplicated skin and skin structure infections caused by Staphylococcus aureus (methicillin-susceptible only) or Streptococcus pyogenes.

Community-acquired pneumonia caused by Streptococcus pneumoniae (including multi-drug resistant strains [MDRSP] [MDRSP refers to isolates resistant to two or more of the following antibiotics: penicillin, second-generation cephalosporins, macrolides, tetracycline, and trimethoprim/sulfamethoxazole.]), including cases with concurrent bacteremia, or Staphylococcus aureus (methicillin-susceptible strains only).

To reduce the development of drug-resistant bacteria and maintain the effectiveness of ZYVOX and other antibacterial drugs, ZYVOX should be used only to treat or prevent infections that are proven or strongly suspected to be caused by susceptible bacteria. When culture and susceptibility information are available, they should be considered in selecting or modifying antibacterial therapy. In the absence of such data, local epidemiology and susceptibility patterns may contribute to the empiric selection of therapy.

CONTRAINDICATIONS

ZYVOX formulations are contraindicated for use in patients who have known hypersensitivity to linezolid or any of the other product components.

Monoamine Oxidase Inhibitors

Linezolid should not be used in patients taking any medicinal product which inhibits monoamine oxidases A or B (e.g., phenelzine, isocarboxazid) or within two weeks of taking any such medicinal product.

Potential Interactions Producing Elevation of Blood Pressure

Unless patients are monitored for potential increases in blood pressure, linezolid should not be administered to patients with uncontrolled hypertension, pheochromocytoma, thyrotoxicosis and/or patients taking any of the following types of medications: directly and indirectly acting sympathomimetic agents (e.g., pseudoephedrine), vasopressive agents (e.g., epinephrine, norepinephrine), dopaminergic agents (e.g., dopamine, dobutamine) (see PRECAUTIONS, Drug Interactions).

Potential Serotonergic Interactions

Unless patients are carefully observed for signs and/or symptoms of serotonin syndrome, linezolid should not be administered to patients with carcinoid syndrome and/or patients taking any of the following medications: serotonin re-uptake inhibitors, tricyclic antidepressants, serotonin 5-HT1 receptor agonists (triptans), meperidine or buspirone (see PRECAUTIONS, General and Drug Interactions).

WARNINGS

Myelosuppression (including anemia, leukopenia, pancytopenia, and thrombocytopenia) has been reported in patients receiving linezolid. In cases where the outcome is known, when linezolid was discontinued, the affected hematologic parameters have risen toward pretreatment levels. Complete blood counts should be monitored weekly in patients who receive linezolid, particularly in those who receive linezolid for longer than two weeks, those with pre-existing myelosuppression, those receiving concomitant drugs that produce bone marrow suppression, or those with a chronic infection who have received previous or concomitant antibiotic therapy. Discontinuation of therapy with linezolid should be considered in patients who develop or have worsening myelosuppression.

In adult and juvenile dogs and rats, myelosuppression, reduced extramedullary hematopoiesis in spleen and liver, and lymphoid depletion of thymus, lymph nodes, and spleen were observed (see ANIMAL PHARMACOLOGY).

Mortality Imbalance in an Investigational Study in Patients with Catheter-Related Bloodstream Infections, including those with catheter-site infections

An imbalance in mortality was seen in patients treated with linezolid relative to vancomycin/dicloxacillin/oxacillin in an open-label study in seriously ill patients with intravascular catheter-related infections [78/363 (21.5%) vs. 58/363 (16.0%); odds ratio 1.426, 95% CI 0.970, 2.098]. While causality has not been established, this observed imbalance occurred primarily in linezolid-treated patients in whom either Gram-negative pathogens, mixed Gram-negative and Gram-positive pathogens, or no pathogen were identified at baseline, but was not seen in patients with Gram-positive infections only.

Linezolid is not approved and should not be used for the treatment of patients with catheter-related bloodstream infections or catheter-site infections.

Linezolid has no clinical activity against Gram-negative pathogens and is not indicated for the treatment of Gram-negative infections. It is critical that specific Gram-negative therapy be initiated immediately if a concomitant Gram-negative pathogen is documented or suspected (see INDICATIONS AND USAGE).

Clostridium difficile associated diarrhea (CDAD) has been reported with use of nearly all antibacterial agents, including ZYVOX, and may range in severity from mild diarrhea to fatal colitis. Treatment with antibacterial agents alters the normal flora of the colon leading to overgrowth of C. difficile.

C. difficile produces toxins A and B which contribute to the development of CDAD. Hypertoxin producing strains of C. difficile cause increased morbidity and mortality, as these infections can be refractory to antimicrobial therapy and may require colectomy. CDAD must be considered in all patients who present with diarrhea following antibiotic use.

Careful medical history is necessary since CDAD has been reported to occur over two months after the administration of antibacterial agents.

If CDAD is suspected or confirmed, ongoing antibiotic use not directed against C. difficile may need to be discontinued. Appropriate fluid and electrolyte management, protein supplementation, antibiotic treatment of C. difficile, and surgical evaluation should be instituted as clinically indicated.

PRECAUTIONS

General

Lactic Acidosis

Lactic acidosis has been reported with the use of ZYVOX. In reported cases, patients experienced repeated episodes of nausea and vomiting. Patients who develop recurrent nausea or vomiting, unexplained acidosis, or a low bicarbonate level while receiving ZYVOX should receive immediate medical evaluation.

Serotonin Syndrome

Spontaneous reports of serotonin syndrome associated with the co-administration of ZYVOX and serotonergic agents, including antidepressants such as selective serotonin reuptake inhibitors (SSRIs), have been reported (see PRECAUTIONS, Drug Interactions).

Where administration of ZYVOX and concomitant serotonergic agents is clinically appropriate, patients should be closely observed for signs and symptoms of serotonin syndrome such as cognitive dysfunction, hyperpyrexia, hyperreflexia and incoordination. If signs or symptoms occur physicians should consider discontinuation of either one or both agents. If the concomitant serotonergic agent is withdrawn, discontinuation symptoms can be observed (see package insert of the specified agent(s) for a description of the associated discontinuation symptoms).

Peripheral and optic neuropathy have been reported in patients treated with ZYVOX, primarily those patients treated for longer than the maximum recommended duration of 28 days. In cases of optic neuropathy that progressed to loss of vision, patients were treated for extended periods beyond the maximum recommended duration. Visual blurring has been reported in some patients treated with ZYVOX for less than 28 days.

If patients experience symptoms of visual impairment, such as changes in visual acuity, changes in color vision, blurred vision, or visual field defect, prompt ophthalmic evaluation is recommended. Visual function should be monitored in all patients taking ZYVOX for extended periods (≥ 3 months) and in all patients reporting new visual symptoms regardless of length of therapy with ZYVOX. If peripheral or optic neuropathy occurs, the continued use of ZYVOX in these patients should be weighed against the potential risks.

Convulsions

Convulsions have been reported in patients when treated with linezolid. In some of these cases, a history of seizures or risk factors for seizures was reported.

The use of antibiotics may promote the overgrowth of nonsusceptible organisms. Should superinfection occur during therapy, appropriate measures should be taken.

ZYVOX has not been studied in patients with uncontrolled hypertension, pheochromocytoma, carcinoid syndrome, or untreated hyperthyroidism.

The safety and efficacy of ZYVOX formulations given for longer than 28 days have not been evaluated in controlled clinical trials.

Prescribing ZYVOX in the absence of a proven or strongly suspected bacterial infection or a prophylactic indication is unlikely to provide benefit to the patient and increases the risk of the development of drug-resistant bacteria.

Information for Patients

Patients should be advised that:

- ZYVOX may be taken with or without food.
- They should inform their physician if they have a history of hypertension.
- Large quantities of foods or beverages with high tyramine content should be avoided while taking ZYVOX. Quantities of tyramine consumed should be less than 100 mg per meal. Foods high in tyramine content include those that may have undergone protein changes by aging, fermentation, pickling, or smoking to improve flavor, such as aged cheeses (0 to 15 mg tyramine per ounce); fermented or air-dried meats (0.1 to 8 mg tyramine per ounce); sauerkraut (8 mg tyramine per 8 ounces); soy sauce (5 mg tyramine per 1 teaspoon); tap beers (4 mg tyramine per 12 ounces); red wines (0 to 6 mg tyramine per 8 ounces). The tyramine content of any protein-rich food may be increased if stored for long periods or improperly refrigerated.^9,10
- They should inform their physician if taking medications containing pseudoephedrine HCl or phenylpropanolamine HCl, such as cold remedies and decongestants.
- They should inform their physician if taking serotonin re-uptake inhibitors or other antidepressants.
- Phenylketonurics: Each 5 mL of the 100 mg/5 mL ZYVOX for Oral Suspension contains 20 mg phenylalanine. The other ZYVOX formulations do not contain phenylalanine. Contact your physician or pharmacist.
- They should inform their physician if they experience changes in vision.
- They should inform their physician if they have a history of seizures.
- Diarrhea is a common problem caused by antibiotics, which usually ends when the antibiotic is discontinued. Sometimes after starting treatment with antibiotics, patients can develop watery and bloody stools (with or without stomach cramps and fever) even as late as two or more months after having taken the last dose of the antibiotic. If this occurs, patients should contact their physician as soon as possible.

Patients should be counseled that antibacterial drugs including ZYVOX should only be used to treat bacterial infections. They do not treat viral infections (e.g., the common cold). When ZYVOX is prescribed to treat a bacterial infection, patients should be told that although it is common to feel better early in the course of therapy, the medication should be taken exactly as directed. Skipping doses or not completing the full course of therapy may (1) decrease the effectiveness of the immediate treatment and (2) increase the likelihood that bacteria will develop resistance and will not be treatable by ZYVOX or other antibacterial drugs in the future.

Drug Interactions

(see also CLINICAL PHARMACOLOGY, Drug-Drug Interactions)

Monoamine Oxidase Inhibition

Linezolid is a reversible, nonselective inhibitor of monoamine oxidase. Therefore, linezolid has the potential for interaction with adrenergic and serotonergic agents.

Adrenergic Agents: Some individuals receiving ZYVOX may experience a reversible enhancement of the pressor response to indirect-acting sympathomimetic agents, vasopressor or dopaminergic agents. Commonly used drugs such as phenylpropanolamine and pseudoephedrine have been specifically studied. Initial doses of adrenergic agents, such as dopamine or epinephrine, should be reduced and titrated to achieve the desired response.

Serotonergic Agents: Co-administration of linezolid and serotonergic agents was not associated with serotonin syndrome in Phase 1, 2 or 3 studies. Spontaneous reports of serotonin syndrome associated with co-administration of ZYVOX and serotonergic agents, including antidepressants such as selective serotonin reuptake inhibitors (SSRIs), have been reported. Patients who are treated with ZYVOX and concomitant serotonergic agents should be closely observed as described in the PRECAUTIONS, General Section.

Strong CYP450 Inducers: In a study in healthy volunteers, co-administration of rifampin with oral linezolid resulted in a 21% decrease in linezolid Cmax and a 32% decrease in linezolid AUC0–12. The clinical significance of this interaction is unknown. Other strong inducers of hepatic enzymes (e.g. carbamazepine, phenytoin, phenobarbital) could cause a similar or smaller decrease in linezolid exposure (see CLINICAL PHARMACOLOGY, Drug-Drug Interactions)

Drug-Laboratory Test Interactions

There are no reported drug-laboratory test interactions.

Carcinogenesis, Mutagenesis, Impairment of Fertility

Lifetime studies in animals have not been conducted to evaluate the carcinogenic potential of linezolid. Neither mutagenic nor clastogenic potential was found in a battery of tests including: assays for mutagenicity (Ames bacterial reversion and CHO cell mutation), an in vitro unscheduled DNA synthesis (UDS) assay, an in vitro chromosome aberration assay in human lymphocytes, and an in vivo mouse micronucleus assay.

Linezolid did not affect the fertility or reproductive performance of adult female rats. It reversibly decreased fertility and reproductive performance in adult male rats when given at doses ≥ 50 mg/kg/day, with exposures approximately equal to or greater than the expected human exposure level (exposure comparisons are based on AUCs). The reversible fertility effects were mediated through altered spermatogenesis. Affected spermatids contained abnormally formed and oriented mitochondria and were non-viable. Epithelial cell hypertrophy and hyperplasia in the epididymis was observed in conjunction with decreased fertility. Similar epididymal changes were not seen in dogs.

In sexually mature male rats exposed to drug as juveniles, mildly decreased fertility was observed following treatment with linezolid through most of their period of sexual development (50 mg/kg/day from days 7 to 36 of age, and 100 mg/kg/day from days 37 to 55 of age), with exposures up to 1.7-fold greater than mean AUCs observed in pediatric patients aged 3 months to 11 years. Decreased fertility was not observed with shorter treatment periods, corresponding to exposure in utero through the early neonatal period (gestation day 6 through postnatal day 5), neonatal exposure (postnatal days 5 to 21), or to juvenile exposure (postnatal days 22 to 35). Reversible reductions in sperm motility and altered sperm morphology were observed in rats treated from postnatal day 22 to 35.

Pregnancy

Teratogenic Effects.

Pregnancy Category C

Linezolid was not teratogenic in mice, rats, or rabbits at exposure levels 6.5-fold (in mice), equivalent to (in rats), or 0.06-fold (in rabbits) the expected human exposure level, based on AUCs. However, embryo and fetal toxicities were seen (see Non-teratogenic Effects). There are no adequate and well-controlled studies in pregnant women. ZYVOX should be used during pregnancy only if the potential benefit justifies the potential risk to the fetus.

Non-teratogenic Effects

In mice, embryo and fetal toxicities were seen only at doses that caused maternal toxicity (clinical signs and reduced body weight gain). A dose of 450 mg/kg/day (6.5-fold the estimated human exposure level based on AUCs) correlated with increased postimplantational embryo death, including total litter loss, decreased fetal body weights, and an increased incidence of costal cartilage fusion.

In rats, mild fetal toxicity was observed at 15 and 50 mg/kg/day (exposure levels 0.22-fold to approximately equivalent to the estimated human exposure, respectively based on AUCs). The effects consisted of decreased fetal body weights and reduced ossification of sternebrae, a finding often seen in association with decreased fetal body weights. Slight maternal toxicity, in the form of reduced body weight gain, was seen at 50 mg/kg/day.

In rabbits, reduced fetal body weight occurred only in the presence of maternal toxicity (clinical signs, reduced body weight gain and food consumption) when administered at a dose of 15 mg/kg/day (0.06-fold the estimated human exposure based on AUCs).

When female rats were treated with 50 mg/kg/day (approximately equivalent to the estimated human exposure based on AUCs) of linezolid during pregnancy and lactation, survival of pups was decreased on postnatal days 1 to 4. Male and female pups permitted to mature to reproductive age, when mated, showed an increase in preimplantation loss.

Nursing Mothers

Linezolid and its metabolites are excreted in the milk of lactating rats. Concentrations in milk were similar to those in maternal plasma. It is not known whether linezolid is excreted in human milk. Because many drugs are excreted in human milk, caution should be exercised when ZYVOX is administered to a nursing woman.

Pediatric Use

The safety and effectiveness of ZYVOX for the treatment of pediatric patients with the following infections are supported by evidence from adequate and well-controlled studies in adults, pharmacokinetic data in pediatric patients, and additional data from a comparator-controlled study of Gram-positive infections in pediatric patients ranging in age from birth through 11 years (see INDICATIONS AND USAGE and CLINICAL STUDIES):

- nosocomial pneumonia
- complicated skin and skin structure infections
- community-acquired pneumonia (also supported by evidence from an uncontrolled study in patients ranging in age from 8 months through 12 years)
- vancomycin-resistant Enterococcus faecium infections

The safety and effectiveness of ZYVOX for the treatment of pediatric patients with the following infection have been established in a comparator-controlled study in pediatric patients ranging in age from 5 through 17 years (see CLINICAL STUDIES):

- uncomplicated skin and skin structure infections caused by Staphylococcus aureus (methicillin-susceptible strains only) or Streptococcus pyogenes

Pharmacokinetic information generated in pediatric patients with ventriculoperitoneal shunts showed variable cerebrospinal fluid (CSF) linezolid concentrations following single and multiple dosing of linezolid; therapeutic concentrations were not consistently achieved or maintained in the CSF. Therefore, the use of linezolid for the empiric treatment of pediatric patients with central nervous system infections is not recommended.

The Cmax and the volume of distribution (Vss) of linezolid are similar regardless of age in pediatric patients. However, linezolid clearance is a function of age. Excluding neonates less than a week of age, clearance is most rapid in the youngest age groups ranging from >1 week old to 11 years, resulting in lower single-dose systemic exposure (AUC) and shorter half-life as compared with adults. As age of pediatric patients increases, the clearance of linezolid gradually decreases, and by adolescence, mean clearance values approach those observed for the adult population. There is wider inter-subject variability in linezolid clearance and in systemic drug exposure (AUC) across all pediatric age groups as compared with adults.

Similar mean daily AUC values were observed in pediatric patients from birth to 11 years of age dosed q8h relative to adolescents or adults dosed q12h. Therefore, the dosage for pediatric patients up to 11 years of age should be 10 mg/kg q8h. Pediatric patients 12 years and older should receive 600 mg q12h.

Recommendations for the dosage regimen for pre-term neonates less than 7 days of age (gestational age less than 34 weeks) are based on pharmacokinetic data from 9 pre-term neonates. Most of these pre-term neonates have lower systemic linezolid clearance values and larger AUC values than many full-term neonates and older infants. Therefore, these pre-term neonates should be initiated with a dosing regimen of 10 mg/kg q12h. Consideration may be given to the use of a 10 mg/kg q8h regimen in neonates with a sub-optimal clinical response. All neonatal patients should receive 10 mg/kg q8h by 7 days of life (see CLINICAL PHARMACOLOGY, Special Populations, Pediatric and DOSAGE AND ADMINISTRATION).

In limited clinical experience, 5 out of 6 (83%) pediatric patients with infections due to Gram-positive pathogens with MICs of 4 µg/mL treated with ZYVOX had clinical cures. However, pediatric patients exhibit wider variability in linezolid clearance and systemic exposure (AUC) compared with adults. In pediatric patients with a sub-optimal clinical response, particularly those with pathogens with MIC of 4 µg/mL, lower systemic exposure, site and severity of infection, and the underlying medical condition should be considered when assessing clinical response (see CLINICAL PHARMACOLOGY, Special Populations, Pediatric and DOSAGE AND ADMINISTRATION).

Geriatric Use

Of the 2046 patients treated with ZYVOX in Phase 3 comparator-controlled clinical trials, 589 (29%) were 65 years or older and 253 (12%) were 75 years or older. No overall differences in safety or effectiveness were observed between these patients and younger patients.

ANIMAL PHARMACOLOGY

Target organs of linezolid toxicity were similar in juvenile and adult rats and dogs. Dose- and time-dependent myelosuppression, as evidenced by bone marrow hypocellularity/decreased hematopoiesis, decreased extramedullary hematopoiesis in spleen and liver, and decreased levels of circulating erythrocytes, leukocytes, and platelets have been seen in animal studies. Lymphoid depletion occurred in thymus, lymph nodes, and spleen. Generally, the lymphoid findings were associated with anorexia, weight loss, and suppression of body weight gain, which may have contributed to the observed effects.

In rats administered linezolid orally for 6 months, non-reversible, minimal to mild axonal degeneration of sciatic nerves was observed at 80 mg/kg/day; minimal degeneration of the sciatic nerve was also observed in 1 male at this dose level at a 3-month interim necropsy. Sensitive morphologic evaluation of perfusion-fixed tissues was conducted to investigate evidence of optic nerve degeneration. Minimal to moderate optic nerve degeneration was evident in 2 male rats after 6 months of dosing, but the direct relationship to drug was equivocal because of the acute nature of the finding and its asymmetrical distribution. The nerve degeneration observed was microscopically comparable to spontaneous unilateral optic nerve degeneration reported in aging rats and may be an exacerbation of common background change.

These effects were observed at exposure levels that are comparable to those observed in some human subjects. The hematopoietic and lymphoid effects were reversible, although in some studies, reversal was incomplete within the duration of the recovery period.

ADVERSE REACTIONS

Adult Patients

The safety of ZYVOX formulations was evaluated in 2046 adult patients enrolled in seven Phase 3 comparator-controlled clinical trials, who were treated for up to 28 days. In these studies, 85% of the adverse events reported with ZYVOX were described as mild to moderate in intensity. Table 6 shows the incidence of adverse events reported in at least 2% of patients in these trials. The most common adverse events in patients treated with ZYVOX were diarrhea (incidence across studies: 2.8% to 11.0%), headache (incidence across studies: 0.5% to 11.3%), and nausea (incidence across studies: 3.4% to 9.6%).

Table 6. Incidence (%) of Adverse Events Reported in ≥2% of Adult Patients in Comparator-Controlled Clinical Trials with ZYVOX
Event | ZYVOX (n=2046) | All Comparators [Comparators included cefpodoxime proxetil 200 mg PO q12h; ceftriaxone 1 g IV q12h; clarithromycin 250 mg PO q12h; dicloxacillin 500 mg PO q6h; oxacillin 2 g IV q6h; vancomycin 1 g IV q12h.] (n=2001)
Diarrhea | 8.3 | 6.3
Headache | 6.5 | 5.5
Nausea | 6.2 | 4.6
Vomiting | 3.7 | 2.0
Insomnia | 2.5 | 1.7
Constipation | 2.2 | 2.1
Rash | 2.0 | 2.2
Dizziness | 2.0 | 1.9
Fever | 1.6 | 2.1

Other adverse events reported in Phase 2 and Phase 3 studies included oral moniliasis, vaginal moniliasis, hypertension, dyspepsia, localized abdominal pain, pruritus, and tongue discoloration.

Table 7 shows the incidence of drug-related adverse events reported in at least 1% of adult patients in these trials by dose of ZYVOX.

Table 7. Incidence (%) of Drug-Related Adverse Events Occurring in >1% of Adult Patients Treated with ZYVOX in Comparator-Controlled Clinical Trials
 | Uncomplicated Skin and Skin Structure Infections |  | All Other Indications
Adverse Event | ZYVOX 400 mg PO q12h (n=548) | Clarithromycin 250 mg PO q12h (n=537) | ZYVOX 600 mg q12h (n=1498) | All Other Comparators [Comparators included cefpodoxime proxetil 200 mg PO q12h; ceftriaxone 1 g IV q12h; dicloxacillin 500 mg PO q6h; oxacillin 2 g IV q6h; vancomycin 1 g IV q12h.] (n=1464)
% of patients with 1 drug-related adverse event | 25.4 | 19.6 | 20.4 | 14.3
% of patients discontinuing due to drug-related adverse events [The most commonly reported drug-related adverse events leading to discontinuation in patients treated with ZYVOX were nausea, headache, diarrhea, and vomiting.] | 3.5 | 2.4 | 2.1 | 1.7
Diarrhea | 5.3 | 4.8 | 4.0 | 2.7
Nausea | 3.5 | 3.5 | 3.3 | 1.8
Headache | 2.7 | 2.2 | 1.9 | 1.0
Taste alteration | 1.8 | 2.0 | 0.9 | 0.2
Vaginal moniliasis | 1.6 | 1.3 | 1.0 | 0.4
Fungal infection | 1.5 | 0.2 | 0.1 | <0.1
Abnormal liver function tests | 0.4 | 0 | 1.3 | 0.5
Vomiting | 0.9 | 0.4 | 1.2 | 0.4
Tongue discoloration | 1.1 | 0 | 0.2 | 0
Dizziness | 1.1 | 1.5 | 0.4 | 0.3
Oral moniliasis | 0.4 | 0 | 1.1 | 0.4

Pediatric Patients

The safety of ZYVOX formulations was evaluated in 215 pediatric patients ranging in age from birth through 11 years, and in 248 pediatric patients aged 5 through 17 years (146 of these 248 were age 5 through 11 and 102 were age 12 to 17). These patients were enrolled in two Phase 3 comparator-controlled clinical trials and were treated for up to 28 days. In these studies, 83% and 99%, respectively, of the adverse events reported with ZYVOX were described as mild to moderate in intensity. In the study of hospitalized pediatric patients (birth through 11 years) with Gram-positive infections, who were randomized 2 to 1 (linezolid:vancomycin), mortality was 6.0% (13/215) in the linezolid arm and 3.0% (3/101) in the vancomycin arm. However, given the severe underlying illness in the patient population, no causality could be established. Table 8 shows the incidence of adverse events reported in at least 2% of pediatric patients treated with ZYVOX in these trials.

Table 8. Incidence (%) of Adverse Events Reported in ≥2% of Pediatric Patients Treated with ZYVOX in Comparator-Controlled Clinical Trials
 | Uncomplicated Skin and Skin Structure Infections [Patients 5 through 11 years of age received ZYVOX 10 mg/kg PO q12h or cefadroxil 15 mg/kg PO q12h. Patients 12 years or older received ZYVOX 600 mg PO q12h or cefadroxil 500 mg PO q12h.] |  | All Other Indications [Patients from birth through 11 years of age received ZYVOX 10 mg/kg IV/PO q8h or vancomycin 10 to 15 mg/kg IV q6–24h, depending on age and renal clearance.]
Event | ZYVOX (n=248) | Cefadroxil (n = 251) | ZYVOX (n = 215) | Vancomycin (n=101)
Fever | 2.9 | 3.6 | 14.1 | 14.1
Diarrhea | 7.8 | 8.0 | 10.8 | 12.1
Vomiting | 2.9 | 6.4 | 9.4 | 9.1
Sepsis | 0 | 0 | 8.0 | 7.1
Rash | 1.6 | 1.2 | 7.0 | 15.2
Headache | 6.5 | 4.0 | 0.9 | 0
Anemia | 0 | 0 | 5.6 | 7.1
Thrombocytopenia | 0 | 0 | 4.7 | 2.0
Upper respiratory infection | 3.7 | 5.2 | 4.2 | 1.0
Nausea | 3.7 | 3.2 | 1.9 | 0
Dyspnea | 0 | 0 | 3.3 | 1.0
Reaction at site of injection or of vascular catheter | 0 | 0 | 3.3 | 5.1
Trauma | 3.3 | 4.8 | 2.8 | 2.0
Pharyngitis | 2.9 | 1.6 | 0.5 | 1.0
Convulsion | 0 | 0 | 2.8 | 2.0
Hypokalemia | 0 | 0 | 2.8 | 3.0
Pneumonia | 0 | 0 | 2.8 | 2.0
Thrombocythemia | 0 | 0 | 2.8 | 2.0
Cough | 2.4 | 4.0 | 0.9 | 0
Generalized abdominal pain | 2.4 | 2.8 | 0.9 | 2.0
Localized abdominal pain | 2.4 | 2.8 | 0.5 | 1.0
Apnea | 0 | 0 | 2.3 | 2.0
Gastrointestinal bleeding | 0 | 0 | 2.3 | 1.0
Generalized edema | 0 | 0 | 2.3 | 1.0
Loose stools | 1.6 | 0.8 | 2.3 | 3.0
Localized pain | 2.0 | 1.6 | 0.9 | 0
Skin disorder | 2.0 | 0 | 0.9 | 1.0

Table 9 shows the incidence of drug-related adverse events reported in more than 1% of pediatric patients (and more than 1 patient) in either treatment group in the comparator-controlled Phase 3 trials.

Table 9. Incidence (%) of Drug-related Adverse Events Occurring in >1% of Pediatric Patients (and >1 Patient) in Either Treatment Group in Comparator-Controlled Clinical Trials
Event | Uncomplicated Skin and Skin Structure Infections [Patients 5 through 11 years of age received ZYVOX 10 mg/kg PO q12h or cefadroxil 15 mg/kg PO q12h. Patients 12 years or older received ZYVOX 600 mg PO q12h or cefadroxil 500 mg PO q12h.] |  | All Other Indications [Patients from birth through 11 years of age received ZYVOX 10 mg/kg IV/PO q8h or vancomycin 10 to 15 mg/kg IV q6–24h, depending on age and renal clearance.]
Event | ZYVOX (n=248) | Cefadroxil (n=251) | ZYVOX (n=215) | Vancomycin (n=101)
% of patients with ≥1 drug-related adverse event | 19.2 | 14.1 | 18.8 | 34.3
% of patients discontinuing due to a drug-related adverse event | 1.6 | 2.4 | 0.9 | 6.1
Diarrhea | 5.7 | 5.2 | 3.8 | 6.1
Nausea | 3.3 | 2.0 | 1.4 | 0
Headache | 2.4 | 0.8 | 0 | 0
Loose stools | 1.2 | 0.8 | 1.9 | 0
Thrombocytopenia | 0 | 0 | 1.9 | 0
Vomiting | 1.2 | 2.4 | 1.9 | 1.0
Generalized abdominal pain | 1.6 | 1.2 | 0 | 0
Localized abdominal pain | 1.6 | 1.2 | 0 | 0
Anemia | 0 | 0 | 1.4 | 1.0
Eosinophilia | 0.4 | 0.4 | 1.4 | 0
Rash | 0.4 | 1.2 | 1.4 | 7.1
Vertigo | 1.2 | 0.4 | 0 | 0
Oral moniliasis | 0 | 0 | 0.9 | 4.0
Fever | 0 | 0 | 0.5 | 3.0
Pruritus at non-application site | 0.4 | 0 | 0 | 2.0
Anaphylaxis | 0 | 0 | 0 | 10.1 [These reports were of 'red-man syndrome', which were coded as anaphylaxis.]

Laboratory Changes

ZYVOX has been associated with thrombocytopenia when used in doses up to and including 600 mg every 12 hours for up to 28 days. In Phase 3 comparator-controlled trials, the percentage of adult patients who developed a substantially low platelet count (defined as less than 75% of lower limit of normal and/or baseline) was 2.4% (range among studies: 0.3 to 10.0%) with ZYVOX and 1.5% (range among studies: 0.4 to 7.0%) with a comparator. In a study of hospitalized pediatric patients ranging in age from birth through 11 years, the percentage of patients who developed a substantially low platelet count (defined as less than 75% of lower limit of normal and/or baseline) was 12.9% with ZYVOX and 13.4% with vancomycin. In an outpatient study of pediatric patients aged from 5 through 17 years, the percentage of patients who developed a substantially low platelet count was 0% with ZYVOX and 0.4% with cefadroxil. Thrombocytopenia associated with the use of ZYVOX appears to be dependent on duration of therapy, (generally greater than 2 weeks of treatment). The platelet counts for most patients returned to the normal range/baseline during the follow-up period. No related clinical adverse events were identified in Phase 3 clinical trials in patients developing thrombocytopenia. Bleeding events were identified in thrombocytopenic patients in a compassionate use program for ZYVOX; the role of linezolid in these events cannot be determined (see WARNINGS).

Changes seen in other laboratory parameters, without regard to drug relationship, revealed no substantial differences between ZYVOX and the comparators. These changes were generally not clinically significant, did not lead to discontinuation of therapy, and were reversible. The incidence of adult and pediatric patients with at least one substantially abnormal hematologic or serum chemistry value is presented in Tables 10, 11, 12, and 13.

Table 10. Percent of Adult Patients who Experienced at Least One Substantially Abnormal [<75% (<50% for neutrophils) of Lower Limit of Normal (LLN) for values normal at baseline; <75% (<50% for neutrophils) of LLN and of baseline for values abnormal at baseline.] Hematology Laboratory Value in Comparator-Controlled Clinical Trials with ZYVOX
Laboratory Assay | Uncomplicated Skin and Skin Structure Infections |  | All Other Indications
Laboratory Assay | ZYVOX 400 mg q12h | Clarithromycin 250 mg q12h | ZYVOX 600 mg q12h | All Other Comparators [Comparators included cefpodoxime proxetil 200 mg PO q12h; ceftriaxone 1 g IV q12h; dicloxacillin 500 mg PO q6h; oxacillin 2 g IV q6h; vancomycin 1 g IV q12h.]
Hemoglobin (g/dL) | 0.9 | 0.0 | 7.1 | 6.6
Platelet count (x 10^3/mm^3) | 0.7 | 0.8 | 3.0 | 1.8
WBC (x 10^3/mm^3) | 0.2 | 0.6 | 2.2 | 1.3
Neutrophils (x 10^3/mm^3) | 0.0 | 0.2 | 1.1 | 1.2

Table 11. Percent of Adult Patients who Experienced at Least One Substantially Abnormal [>2 x Upper Limit of Normal (ULN) for values normal at baseline; >2 x ULN and >2 x baseline for values abnormal at baseline.] Serum Chemistry Laboratory Value in Comparator-Controlled Clinical Trials with ZYVOX
Laboratory Assay | Uncomplicated Skin and Skin Structure Infections |  | All Other Indications
Laboratory Assay | ZYVOX 400 mg q12h | Clarithromycin 250 mg q12h | ZYVOX 600 mg q12h | All Other Comparators [Comparators included cefpodoxime proxetil 200 mg PO q12h; ceftriaxone 1 g IV q12h; dicloxacillin 500 mg PO q6h; oxacillin 2 g IV q6h; vancomycin 1 g IV q12h.]
AST (U/L) | 1.7 | 1.3 | 5.0 | 6.8
ALT (U/L) | 1.7 | 1.7 | 9.6 | 9.3
LDH (U/L) | 0.2 | 0.2 | 1.8 | 1.5
Alkaline phosphatase (U/L) | 0.2 | 0.2 | 3.5 | 3.1
Lipase (U/L) | 2.8 | 2.6 | 4.3 | 4.2
Amylase (U/L) | 0.2 | 0.2 | 2.4 | 2.0
Total bilirubin (mg/dL) | 0.2 | 0.0 | 0.9 | 1.1
BUN (mg/dL) | 0.2 | 0.0 | 2.1 | 1.5
Creatinine (mg/dL) | 0.2 | 0.0 | 0.2 | 0.6

Table 12. Percent of Pediatric Patients who Experienced at Least One Substantially Abnormal [<75% (<50% for neutrophils) of Lower Limit of Normal (LLN) for values normal at baseline; <75% (<50% for neutrophils) of LLN and <75% (<50% for neutrophils, <90% for hemoglobin if baseline <LLN) of baseline for values abnormal at baseline.] Hematology Laboratory Value in Comparator-Controlled Clinical Trials with ZYVOX
Laboratory Assay | Uncomplicated Skin and Skin Structure Infections [Patients 5 through 11 years of age received ZYVOX 10 mg/kg PO q12h or cefadroxil 15 mg/kg PO q12h. Patients 12 years or older received ZYVOX 600 mg PO q12h or cefadroxil 500 mg PO q12h.] |  | All Other Indications [Patients from birth through 11 years of age received ZYVOX 10 mg/kg IV/PO q8h or vancomycin 10 to 15 mg/kg IV q6–24h, depending on age and renal clearance.]
Laboratory Assay | ZYVOX | Cefadroxil | ZYVOX | Vancomycin
Hemoglobin (g/dL) | 0.0 | 0.0 | 15.7 | 12.4
Platelet count (x 10^3/mm^3) | 0.0 | 0.4 | 12.9 | 13.4
WBC (x 10^3/mm^3) | 0.8 | 0.8 | 12.4 | 10.3
Neutrophils (x 10^3/mm^3) | 1.2 | 0.8 | 5.9 | 4.3

Table 13. Percent of Pediatric Patients who Experienced at Least One Substantially Abnormal [>2 x Upper Limit of Normal (ULN) for values normal at baseline; >2 x ULN and >2 (>1.5 for total bilirubin) x baseline for values abnormal at baseline.] Serum Chemistry Laboratory Value in Comparator-Controlled Clinical Trials with ZYVOX
Laboratory Assay | Uncomplicated Skin and Skin Structure Infections [Patients 5 through 11 years of age received ZYVOX 10 mg/kg PO q12h or cefadroxil 15 mg/kg PO q12h. Patients 12 years or older received ZYVOX 600 mg PO q12h or cefadroxil 500 mg PO q12h.] |  | All Other Indications [Patients from birth through 11 years of age received ZYVOX 10 mg/kg IV/PO q8h or vancomycin 10 to 15 mg/kg IV q6–24h, depending on age and renal clearance.]
Laboratory Assay | ZYVOX | Cefadroxil | ZYVOX | Vancomycin
ALT (U/L) | 0.0 | 0.0 | 10.1 | 12.5
Lipase (U/L) | 0.4 | 1.2 | --- | ---
Amylase (U/L) | --- | --- | 0.6 | 1.3
Total bilirubin (mg/dL) | --- | --- | 6.3 | 5.2
Creatinine (mg/dL) | 0.4 | 0.0 | 2.4 | 1.0

Postmarketing Experience

Myelosuppression (including anemia, leukopenia, pancytopenia, and thrombocytopenia) has been reported during postmarketing use of ZYVOX (see WARNINGS). Peripheral neuropathy, and optic neuropathy sometimes progressing to loss of vision, have been reported in patients treated with ZYVOX. Lactic acidosis has been reported with the use of ZYVOX (see PRECAUTIONS). Although these reports have primarily been in patients treated for longer than the maximum recommended duration of 28 days, these events have also been reported in patients receiving shorter courses of therapy. Serotonin syndrome has been reported in patients receiving concomitant serotonergic agents, including antidepressants such as selective serotonin reuptake inhibitors (SSRIs) and ZYVOX (see PRECAUTIONS). Convulsions have been reported with the use of ZYVOX (see PRECAUTIONS). Anaphylaxis, angioedema, and bullous skin disorders such as those described as Stevens Johnson syndrome have been reported. Superficial tooth discoloration and tongue discoloration have been reported with the use of linezolid. The tooth discoloration was removable with professional dental cleaning (manual descaling) in cases with known outcome. These events have been chosen for inclusion due to either their seriousness, frequency of reporting, possible causal connection to ZYVOX, or a combination of these factors. Because they are reported voluntarily from a population of unknown size, estimates of frequency cannot be made and causal relationship cannot be precisely established.

OVERDOSAGE

In the event of overdosage, supportive care is advised, with maintenance of glomerular filtration. Hemodialysis may facilitate more rapid elimination of linezolid. In a Phase 1 clinical trial, approximately 30% of a dose of linezolid was removed during a 3-hour hemodialysis session beginning 3 hours after the dose of linezolid was administered. Data are not available for removal of linezolid with peritoneal dialysis or hemoperfusion. Clinical signs of acute toxicity in animals were decreased activity and ataxia in rats and vomiting and tremors in dogs treated with 3000 mg/kg/day and 2000 mg/kg/day, respectively.

DOSAGE AND ADMINISTRATION

The recommended dosage for ZYVOX formulations for the treatment of infections is described in Table 14.

Table 14. Dosage Guidelines for ZYVOX
Infection [Due to the designated pathogens (see INDICATIONS AND USAGE)] | Dosage and Route of Administration |  | Recommended Duration of Treatment (consecutive days)
Infection [Due to the designated pathogens (see INDICATIONS AND USAGE)] | Pediatric Patients [Neonates <7 days: Most pre-term neonates < 7 days of age (gestational age < 34 weeks) have lower systemic linezolid clearance values and larger AUC values than many full-term neonates and older infants. These neonates should be initiated with a dosing regimen of 10 mg/kg q12h. Consideration may be given to the use of 10 mg/kg q8h regimen in neonates with a sub-optimal clinical response. All neonatal patients should receive 10 mg/kg q8h by 7 days of life (see CLINICAL PHARMACOLOGY, Special Populations, Pediatric).] (Birth through 11 Years of Age) | Adults and Adolescents (12 Years and Older) | Recommended Duration of Treatment (consecutive days)
Complicated skin and skin structure infections | 10 mg/kg IV or oral [Oral dosing using either ZYVOX Tablets or ZYVOX for Oral Suspension] q8h | 600 mg IV or oral q12h | 10 to 14
Community-acquired pneumonia, including concurrent bacteremia | 10 mg/kg IV or oral [Oral dosing using either ZYVOX Tablets or ZYVOX for Oral Suspension] q8h | 600 mg IV or oral q12h | 10 to 14
Nosocomial pneumonia | 10 mg/kg IV or oral [Oral dosing using either ZYVOX Tablets or ZYVOX for Oral Suspension] q8h | 600 mg IV or oral q12h | 10 to 14
Vancomycin-resistant Enterococcus faecium infections, including concurrent bacteremia | 10 mg/kg IV or oral q8h | 600 mg IV or oral q12h | 14 to 28
Uncomplicated skin and skin structure infections | <5 yrs: 10 mg/kg oral q8h 5–11 yrs: 10 mg/kg oral q12h | Adults: 400 mg oral q12h Adolescents: 600 mg oral q12h | 10 to 14

Adult patients with infection due to MRSA should be treated with ZYVOX 600 mg q12h.

In limited clinical experience, 5 out of 6 (83%) pediatric patients with infections due to Gram-positive pathogens with MICs of 4 µg/mL treated with ZYVOX had clinical cures. However, pediatric patients exhibit wider variability in linezolid clearance and systemic exposure (AUC) compared with adults. In pediatric patients with a sub-optimal clinical response, particularly those with pathogens with MIC of 4 µg/mL, lower systemic exposure, site and severity of infection, and the underlying medical condition should be considered when assessing clinical response (see CLINICAL PHARMACOLOGY, Special Populations, Pediatric and PRECAUTIONS, Pediatric Use).

In controlled clinical trials, the protocol-defined duration of treatment for all infections ranged from 7 to 28 days. Total treatment duration was determined by the treating physician based on site and severity of the infection, and on the patient's clinical response.

No dose adjustment is necessary when switching from intravenous to oral administration. Patients whose therapy is started with ZYVOX I.V. Injection may be switched to either ZYVOX Tablets or Oral Suspension at the discretion of the physician, when clinically indicated.

Intravenous Administration

ZYVOX I.V. Injection is supplied in single-use, ready-to-use infusion bags (see HOW SUPPLIED for container sizes). Parenteral drug products should be inspected visually for particulate matter prior to administration. Check for minute leaks by firmly squeezing the bag. If leaks are detected, discard the solution, as sterility may be impaired.

ZYVOX I.V. Injection should be administered by intravenous infusion over a period of 30 to 120 minutes. Do not use this intravenous infusion bag in series connections. Additives should not be introduced into this solution. If ZYVOX I.V. Injection is to be given concomitantly with another drug, each drug should be given separately in accordance with the recommended dosage and route of administration for each product. In particular, physical incompatibilities resulted when ZYVOX I.V. Injection was combined with the following drugs during simulated Y-site administration: amphotericin B, chlorpromazine HCl, diazepam, pentamidine isothionate, erythromycin lactobionate, phenytoin sodium, and trimethoprim-sulfamethoxazole. Additionally, chemical incompatibility resulted when ZYVOX I.V. Injection was combined with ceftriaxone sodium.

If the same intravenous line is used for sequential infusion of several drugs, the line should be flushed before and after infusion of ZYVOX I.V. Injection with an infusion solution compatible with ZYVOX I.V. Injection and with any other drug(s) administered via this common line (see Compatible Intravenous Solutions).

Compatible Intravenous Solutions

- 5% Dextrose Injection, USP
- 0.9% Sodium Chloride Injection, USP
- Lactated Ringer's Injection, USP

Keep the infusion bags in the overwrap until ready to use. Store at room temperature. Protect from freezing. ZYVOX I.V. Injection may exhibit a yellow color that can intensify over time without adversely affecting potency.

Constitution of Oral Suspension

ZYVOX for Oral Suspension is supplied as a powder/granule for constitution. Gently tap bottle to loosen powder. Add a total of 123 mL distilled water in two portions. After adding the first half, shake vigorously to wet all of the powder. Then add the second half of the water and shake vigorously to obtain a uniform suspension. After constitution, each 5 mL of the suspension contains 100 mg of linezolid. Before using, gently mix by inverting the bottle 3 to 5 times. DO NOT SHAKE. Store constituted suspension at room temperature. Use within 21 days after constitution.

HOW SUPPLIED

Tablets

ZYVOX Tablets are available as follows:

600 mg (white, capsule-shaped, film-coated tablets printed with "ZYVOX 600 mg")

20 tablets in HDPE bottle | NDC 21695-399-20

Storage of ZYVOX Formulations

Store at 25°C (77°F); excursions permitted to 15–30°C (59–86°F) [see USP Controlled Room Temperature]. Protect from light. Keep bottles tightly closed to protect from moisture. It is recommended that the infusion bags be kept in the overwrap until ready to use. Protect infusion bags from freezing.

CLINICAL STUDIES

Adults

Vancomycin-Resistant Enterococcal Infections

Adult patients with documented or suspected vancomycin-resistant enterococcal infection were enrolled in a randomized, multi-center, double-blind trial comparing a high dose of ZYVOX (600 mg) with a low dose of ZYVOX (200 mg) given every 12 hours (q12h) either intravenously (IV) or orally for 7 to 28 days. Patients could receive concomitant aztreonam or aminoglycosides. There were 79 patients randomized to high-dose linezolid and 66 to low-dose linezolid. The intent-to-treat (ITT) population with documented vancomycin-resistant enterococcal infection at baseline consisted of 65 patients in the high-dose arm and 52 in the low-dose arm.

The cure rates for the ITT population with documented vancomycin-resistant enterococcal infection at baseline are presented in Table 15 by source of infection. These cure rates do not include patients with missing or indeterminate outcomes. The cure rate was higher in the high-dose arm than in the low-dose arm, although the difference was not statistically significant at the 0.05 level.

Table 15. Cure Rates at the Test-of-Cure Visit for ITT Adult Patients with Documented Vancomycin-Resistant Enterococcal Infections at Baseline
Source of Infection | Cured
Source of Infection | ZYVOX 600 mg q12h n/N (%) | ZYVOX 200 mg q12h n/N (%)
Any site | 39/58 (67) | 24/46 (52)
Any site with associated bacteremia | 10/17 (59) | 4/14 (29)
Bacteremia of unknown origin | 5/10 (50) | 2/7 (29)
Skin and skin structure | 9/13 (69) | 5/5 (100)
Urinary tract | 12/19 (63) | 12/20 (60)
Pneumonia | 2/3 (67) | 0/1 (0)
Other [Includes sources of infection such as hepatic abscess, biliary sepsis, necrotic gall bladder, pericolonic abscess, pancreatitis, and catheter-related infection.] | 11/13 (85) | 5/13 (39)

Nosocomial Pneumonia

Adult patients with clinically and radiologically documented nosocomial pneumonia were enrolled in a randomized, multi-center, double-blind trial. Patients were treated for 7 to 21 days. One group received ZYVOX I.V. Injection 600 mg q12h, and the other group received vancomycin 1 g q12h IV. Both groups received concomitant aztreonam (1 to 2 g every 8 hours IV), which could be continued if clinically indicated. There were 203 linezolid-treated and 193 vancomycin-treated patients enrolled in the study. One hundred twenty-two (60%) linezolid-treated patients and 103 (53%) vancomycin-treated patients were clinically evaluable. The cure rates in clinically evaluable patients were 57% for linezolid-treated patients and 60% for vancomycin-treated patients. The cure rates in clinically evaluable patients with ventilator-associated pneumonia were 47% for linezolid-treated patients and 40% for vancomycin-treated patients. A modified intent-to-treat (MITT) analysis of 94 linezolid-treated patients and 83 vancomycin-treated patients included subjects who had a pathogen isolated before treatment. The cure rates in the MITT analysis were 57% in linezolid-treated patients and 46% in vancomycin-treated patients. The cure rates by pathogen for microbiologically evaluable patients are presented in Table 16.

Table 16. Cure Rates at the Test-of-Cure Visit for Microbiologically Evaluable Adult Patients with Nosocomial Pneumonia
Pathogen | Cured
Pathogen | ZYVOX n/N (%) | Vancomycin n/N (%)
Staphylococcus aureus | 23/38 (61) | 14/23 (61)
Methicillin-resistant S. aureus | 13/22 (59) | 7/10 (70)
Streptococcus pneumoniae | 9/9 (100) | 9/10 (90)

Pneumonia caused by multi-drug resistant S.pneumoniae (MDRSP [MDRSP refers to isolates resistant to two or more of the following antibiotics: penicillin, second-generation cephalosporins, macrolides, tetracycline, and trimethoprim/sulfamethoxazole.])

ZYVOX was studied for the treatment of community-acquired (CAP) and hospital-acquired (HAP) pneumonia due to MDRSP by pooling clinical data from seven comparative and non-comparative Phase 2 and Phase 3 studies involving adult and pediatric patients. The pooled MITT population consisted of all patients with S.pneumoniae isolated at baseline; the pooled ME population consisted of patients satisfying criteria for microbiologic evaluability. The pooled MITT population with CAP included 15 patients (41%) with severe illness (risk classes IV and V) as assessed by a prediction rule^11. The pooled clinical cure rates for patients with CAP due to MDRSP were 35/48 (73%) in the MITT and 33/36 (92%) in the ME populations respectively. The pooled clinical cure rates for patients with HAP due to MDRSP were 12/18 (67%) in the MITT and 10/12 (83%) in the ME populations respectively.

Table 17. Clinical cure rates for 36 microbiologically-evaluable patients with CAP due to MDRSP who were treated with ZYVOX (stratified by antibiotic susceptibility)
Susceptibility Screening | Clinical Cure
Susceptibility Screening | n/N [n= pooled number of patients treated successfully; N= pooled number of patients having MDRSP isolates that exhibited resistance to the listed antibiotic] | (%)
Penicillin-resistant | 14/16 | 88
2nd generation cephalosporin-resistant [2nd-generation cephalosporin tested was cefuroxime] | 19/22 | 86
Macrolide-resistant [macrolide tested was erythromycin] | 29/30 | 97
Tetracycline-resistant | 22/24 | 92
Trimethoprim/sulfamethoxazole-resistant | 18/21 | 86

Complicated Skin and Skin Structure Infections

Adult patients with clinically documented complicated skin and skin structure infections were enrolled in a randomized, multi-center, double-blind, double-dummy trial comparing study medications administered IV followed by medications given orally for a total of 10 to 21 days of treatment. One group of patients received ZYVOX I.V. Injection 600 mg q12h followed by ZYVOX Tablets 600 mg q12h; the other group received oxacillin 2 g every 6 hours (q6h) IV followed by dicloxacillin 500 mg q6h orally. Patients could receive concomitant aztreonam if clinically indicated. There were 400 linezolid-treated and 419 oxacillin-treated patients enrolled in the study. Two hundred forty-five (61%) linezolid-treated patients and 242 (58%) oxacillin-treated patients were clinically evaluable. The cure rates in clinically evaluable patients were 90% in linezolid-treated patients and 85% in oxacillin-treated patients. A modified intent-to-treat (MITT) analysis of 316 linezolid-treated patients and 313 oxacillin-treated patients included subjects who met all criteria for study entry. The cure rates in the MITT analysis were 86% in linezolid-treated patients and 82% in oxacillin-treated patients. The cure rates by pathogen for microbiologically evaluable patients are presented in Table 18.

Table 18. Cure Rates at the Test-of-Cure Visit for Microbiologically Evaluable Adult Patients with Complicated Skin and Skin Structure Infections
Pathogen | Cured
Pathogen | ZYVOX n/N (%) | Oxacillin/Dicloxacillin n/N (%)
Staphylococcus aureus | 73/83 (88) | 72/84 (86)
Methicillin-resistant S. aureus | 2/3 (67) | 0/0 (-)
Streptococcus agalactiae | 6/6 (100) | 3/6 (50)
Streptococcus pyogenes | 18/26 (69) | 21/28 (75)

A separate study provided additional experience with the use of ZYVOX in the treatment of methicillin-resistant Staphylococcus aureus (MRSA) infections. This was a randomized, open-label trial in hospitalized adult patients with documented or suspected MRSA infection.

One group of patients received ZYVOX I.V. Injection 600 mg q12h followed by ZYVOX Tablets 600 mg q12h. The other group of patients received vancomycin 1 g q12h IV. Both groups were treated for 7 to 28 days, and could receive concomitant aztreonam or gentamicin if clinically indicated. The cure rates in microbiologically evaluable patients with MRSA skin and skin structure infection were 26/33 (79%) for linezolid-treated patients and 24/33 (73%) for vancomycin-treated patients.

Diabetic Foot Infections

Adult diabetic patients with clinically documented complicated skin and skin structure infections ("diabetic foot infections") were enrolled in a randomized (2:1 ratio), multi-center, open-label trial comparing study medications administered IV or orally for a total of 14 to 28 days of treatment. One group of patients received ZYVOX 600 mg q12h IV or orally; the other group received ampicillin/sulbactam 1.5 to 3 g IV or amoxicillin/clavulanate 500 to 875 mg every 8 to 12 hours (q8–12h) orally. In countries where ampicillin/sulbactam is not marketed, amoxicillin/clavulanate 500 mg to 2 g every 6 hours (q6h) was used for the intravenous regimen. Patients in the comparator group could also be treated with vancomycin 1 g q12h IV if MRSA was isolated from the foot infection. Patients in either treatment group who had Gram-negative bacilli isolated from the infection site could also receive aztreonam 1 to 2 g q8–12h IV. All patients were eligible to receive appropriate adjunctive treatment methods, such as debridement and off-loading, as typically required in the treatment of diabetic foot infections, and most patients received these treatments. There were 241 linezolid-treated and 120 comparator-treated patients in the intent-to-treat (ITT) study population. Two hundred twelve (86%) linezolid-treated patients and 105 (85%) comparator-treated patients were clinically evaluable. In the ITT population, the cure rates were 68.5% (165/241) in linezolid-treated patients and 64% (77/120) in comparator-treated patients, where those with indeterminate and missing outcomes were considered failures. The cure rates in the clinically evaluable patients (excluding those with indeterminate and missing outcomes) were 83% (159/192) and 73% (74/101) in the linezolid- and comparator-treated patients, respectively. A critical post-hoc analysis focused on 121 linezolid-treated and 60 comparator-treated patients who had a Gram-positive pathogen isolated from the site of infection or from blood, who had less evidence of underlying osteomyelitis than the overall study population, and who did not receive prohibited antimicrobials. Based upon that analysis, the cure rates were 71% (86/121) in the linezolid-treated patients and 63% (38/60) in the comparator-treated patients. None of the above analyses were adjusted for the use of adjunctive therapies. The cure rates by pathogen for microbiologically evaluable patients are presented in Table 19.

Table 19. Cure Rates at the Test-of-Cure Visit for Microbiologically Evaluable Adult Patients with Diabetic Foot Infections
Pathogen | Cured
Pathogen | ZYVOX n/N (%) | Comparator n/N (%)
Staphylococcus aureus | 49/63 (78) | 20/29 (69)
Methicillin-resistant S. aureus | 12/17 (71) | 2/3 (67)
Streptococcus agalactiae | 25/29 (86) | 9/16 (56)

Pediatric Patients

Infections Due to Gram-positive Organisms

A safety and efficacy study provided experience on the use of ZYVOX in pediatric patients for the treatment of nosocomial pneumonia, complicated skin and skin structure infections, catheter-related bacteremia, bacteremia of unidentified source, and other infections due to Gram-positive bacterial pathogens, including methicillin-resistant and -susceptible Staphylococcus aureus and vancomycin-resistant Enterococcus faecium. Pediatric patients ranging in age from birth through 11 years with infections caused by the documented or suspected Gram-positive organisms were enrolled in a randomized, open-label, comparator-controlled trial. One group of patients received ZYVOX I.V. Injection 10 mg/kg every 8 hours (q8h) followed by ZYVOX for Oral Suspension 10 mg/kg q8h. A second group received vancomycin 10 to 15 mg/kg IV every 6 to 24 hours, depending on age and renal clearance. Patients who had confirmed VRE infections were placed in a third arm of the study and received ZYVOX 10 mg/kg q8h IV and/or orally. All patients were treated for a total of 10 to 28 days and could receive concomitant Gram-negative antibiotics if clinically indicated. In the intent-to-treat (ITT) population, there were 206 patients randomized to linezolid and 102 patients randomized to vancomycin. One hundred seventeen (57 %) linezolid-treated patients and 55 (54%) vancomycin-treated patients were clinically evaluable. The cure rates in ITT patients were 81% in patients randomized to linezolid and 83% in patients randomized to vancomycin (95% Confidence Interval of the treatment difference; -13%, 8%). The cure rates in clinically evaluable patients were 91% in linezolid-treated patients and 91% in vancomycin-treated patients (95% CI; -11%, 11%). Modified intent-to-treat (MITT) patients included ITT patients who, at baseline, had a Gram-positive pathogen isolated from the site of infection or from blood. The cure rates in MITT patients were 80% in patients randomized to linezolid and 90% in patients randomized to vancomycin (95% CI; -23%, 3%). The cure rates for ITT, MITT, and clinically evaluable patients are presented in Table 20. After the study was completed, 13 additional patients ranging from 4 days through 16 years of age were enrolled in an open-label extension of the VRE arm of the study. Table 21 provides clinical cure rates by pathogen for microbiologically evaluable patients including microbiologically evaluable patients with vancomycin-resistant Enterococcus faecium from the extension of this study.

Table 20. Cure Rates at the Test-of-Cure Visit for Intent to Treat, Modified Intent to Treat, and Clinically Evaluable Pediatric Patients by Baseline Diagnosis
Population | ITT |  | MITT [MITT = ITT patients with an isolated Gram-positive pathogen at baseline] |  | Clinically Evaluable
Population | ZYVOX n/N (%) | Vancomycin n/N (%) | ZYVOX n/N (%) | Vancomycin n/N (%) | ZYVOX n/N (%) | Vancomycin n/N (%)
Any diagnosis | 150/186 (81) | 69/83 (83) | 86/108 (80) | 44/49 (90) | 106/117 (91) | 49/54 (91)
Bacteremia of unidentified source | 22/29 (76) | 11/16 (69) | 8/12 (67) | 7/8 (88) | 14/17 (82) | 7/9 (78)
Catheter-related bacteremia | 30/41 (73) | 8/12 (67) | 25/35 (71) | 7/10 (70) | 21/25(84) | 7/9 (78)
Complicated skin and skin structure infections | 61/72 (85) | 31/34 (91) | 37/43 (86) | 22/23 (96) | 46/49 (94) | 26/27 (96)
Nosocomial pneumonia | 13/18 (72) | 11/12 (92) | 5/6 (83) | 4/4 (100) | 7/7 (100) | 5/5 (100)
Other infections | 24/26 (92) | 8/9 (89) | 11/12 (92) | 4/4 (100) | 18/19 (95) | 4/4 (100)

Table 21. Cure Rates at the Test-of-Cure Visit for Microbiologically Evaluable Pediatric Patients with Infections due to Gram-positive Pathogens
Pathogen | Microbiologically Evaluable
Pathogen | ZYVOX n/N (%) | Vancomycin n/N (%)
Vancomycin-resistant Enterococcus faecium | 6/8 (75) [Includes data from 7 patients enrolled in the open-label extension of this study.] | 0/0 (-)
Staphylococcus aureus | 36/38 (95) | 23/24 (96)
Methicillin-resistant S. aureus | 16/17 (94) | 9/9 (100)
Streptococcus pyogenes | 2/2 (100) | 1/2 (50)

REFERENCES

1. Gonzales RD, PC Schreckenberger, MB Graham, et al. Infections due to vancomycin-resistant Enterococcus faecium resistant to linezolid. The Lancet 2001;357:1179.
2. Herrero IA, NC Issa, R Patel. Nosocomial spread of linezolid-resistant, vancomycin-resistant Enterococcus faecium. The New England Journal of Medicine 2002;346:867–869.
3. Tsiodras S, HS Gold, G Sakoulas, et al. Linezolid resistance in a clinical isolate of Staphylococcus aureus. The Lancet 2001;358:207–208.
4. Goldman DA, RA Weinstein, RP Wenzel, et al. Strategies to prevent and control the emergence and spread of antimicrobial-resistant microorganisms in hospitals. A challenge to hospital leadership. The Journal of the American Medical Association 1996;275:234–240.
5. Centers for Disease Control and Prevention. Guideline for hand hygiene in health-care settings: Recommendations of the Healthcare Infection Control Practices Advisory Committee and the HIPAC/SHEA/APIC/IDSA Hand Hygiene Task Force. Morbidity and Mortality Weekly Report 2002;51 (RR-16).
6. National Committee for Clinical Laboratory Standards. Methods for Dilution Antimicrobial Susceptibility Tests for Bacteria that Grow Aerobically. Fifth Edition. Approved Standard NCCLS Document M7-A5, Vol. 20, No. 2, NCCLS, Wayne, PA, January 2000.
7. National Committee for Clinical Laboratory Standards. Twelfth Informational Supplement. Approved NCCLS Document M100-S12, Vol. 21, No. 1, NCCLS, Wayne, PA, January 2002.
8. National Committee for Clinical Laboratory Standards. Performance Standards for Antimicrobial Disk Susceptibility Tests. Seventh Edition. Approved Standard NCCLS Document M2-A7, Vol. 20, No. 1, NCCLS, Wayne, PA, January 2000.
9. Walker SE et al. Tyramine content of previously restricted foods in monoamine oxidase inhibitor diets. Journal of Clinical Psychopharmacology 1996;16(5):383–388.
10. DaPrada M et al. On tyramine, food, beverages and the reversible MAO inhibitor moclobemide. Journal of Neural Transmission 1988; [Supplement] 26:31–56.
11. Fine MJ, Auble TE, Yealy DM, et al. A Prediction Rule to Identify Low-Risk Patients with Community-Acquired Pneumonia. The New England Journal of Medicine. 1997;336 (4):243–250.

Rx only

LAB-0139-19.0

December 2009

PRINCIPAL DISPLAY PANEL - 600 mg Tablet Bottle Label

NDC 21695-399-20

20 Tablets
Rx only

ZYVOX®
(linezolid) tablets

600 mg

Pfizer
Distributed by
Pharmacia & Upjohn Co
Division of Pfizer Inc, NY, NY 10017

Repackaged by:

Rebel Distributors Corp

Thousand Oaks, CA 91320